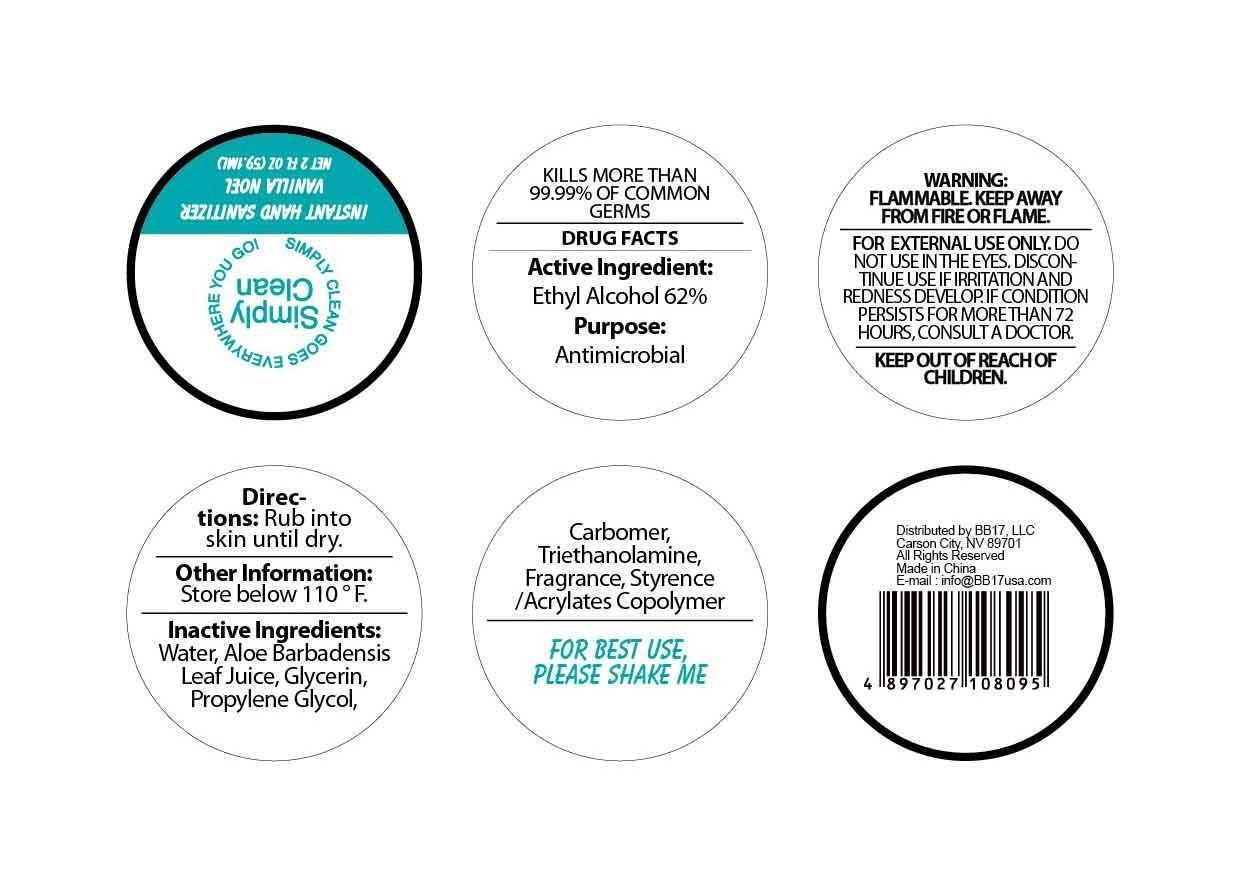 DRUG LABEL: Instant Hand Sanitizer Vanilla Noel
NDC: 53603-1008 | Form: GEL
Manufacturer: BB17, LLC
Category: otc | Type: HUMAN OTC DRUG LABEL
Date: 20130516

ACTIVE INGREDIENTS: Alcohol 62 mL/100 mL
INACTIVE INGREDIENTS: WATER; ALOE; ALOE VERA LEAF; GLYCERIN; PROPYLENE GLYCOL; CARBOMER HOMOPOLYMER TYPE C (ALLYL PENTAERYTHRITOL CROSSLINKED); TROLAMINE; STYRENE

Active Ingredient

Ethyl Alcohol 62%

Purpose
Antimicrobial

INDICATIONS AND USAGE

KILLS MORE THAN 99.99% OF COMMON GERMS

WARNING:

Flammable;

Keep away from fire or flame;

FOR EXTERNAL USE ONLY;

DO NOT USE IN THE EYES.

DISCONTINUE USE IF IRRITATION AND REDNESS DEVELOP.

IF CONDITION PERSISTS FOR MORE THAN 72 HOURS, CONSULT A DOCTOR.

Keep out of reach of children.

DIRECTIONS:

Rub into skin until dry.

Other Information:

Store below 110 F.

INACTIVE INGREDIENTS:
Water, Aloe barbadenis, Leaf Juice, Glycerin,
Propylene Glycol, Carbomer, Triethanolamine, Fragrance, Styrene/Acrylates Copolymer